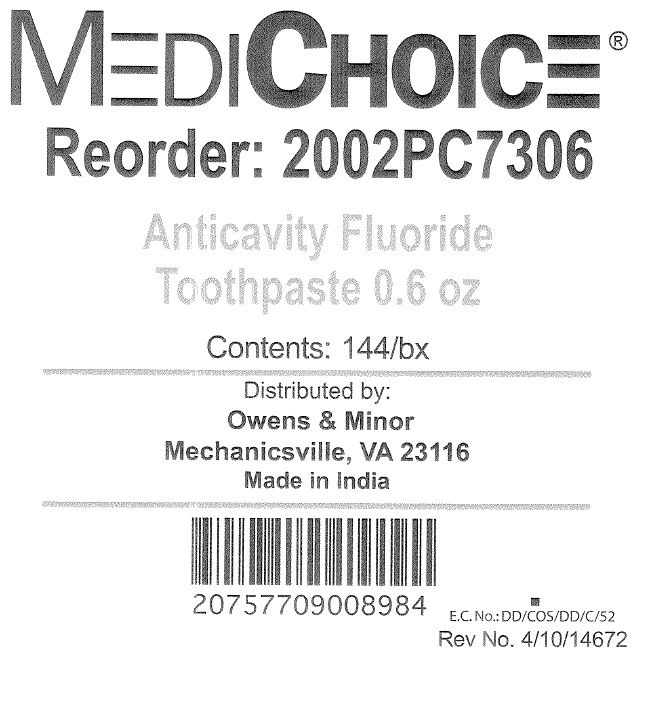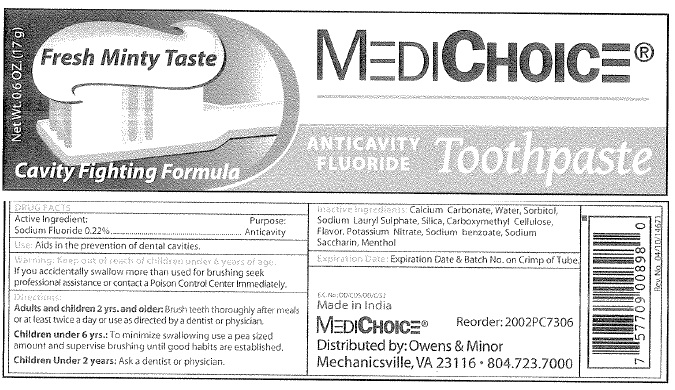 DRUG LABEL: MEDICHOICE ANTICAVITY FLUORIDE
NDC: 39892-0601 | Form: PASTE, DENTIFRICE
Manufacturer: Owens and Minor
Category: otc | Type: HUMAN OTC DRUG LABEL
Date: 20111025

ACTIVE INGREDIENTS: SODIUM FLUORIDE 22 g/100 g
INACTIVE INGREDIENTS: CALCIUM CARBONATE; WATER; SORBITOL; SODIUM LAURYL SULFATE; SILICON DIOXIDE; CARBOXYMETHYLCELLULOSE; POTASSIUM NITRATE; SODIUM BENZOATE; SACCHARIN SODIUM; MENTHOL

MEDICHOICE ANTICAVITY FLUORIDE TOOTHPASTE

Active Ingredient

Sodium Fluoride 0.22%

Purpose

Anticavity

Use:

Aids in the prevention of dental cavities.

Directions

Adults and children 2 yrs and older: Brush teeth thoroughly after meals or at least twice a day or use as directed by a dentist or physician.

Children under 6 yrs: To minimize swallowing use a pea-sized amount and supervise brushing until good habits are established.

Children under 2 years: Ask a dentist or physician.

Warning

If you accidentally swallow more than used for brushing seek professional assistance or contact a Poison Control Center Immediately.

Keep out of reach of children

under 6 years of age.

Inactive Ingredients

Calcium Carbonate, Water, Sorbitol, Sodium Lauryl Sulfate, Silica, Carboxymethyl Cellulose, Flavor, Potassium Nitrate, Sodium benzoate, Sodium saccharin, menthol

Expiration Date: Expiration Date and Batch No. on crimp of Tube

E.c No.: DD/COS/DD/C/52

Made in India

MediChoice Reorder: 2002PC7306

Distributed by: Owens and Minor

Mechanicsville, VA 23116 804.723.7000